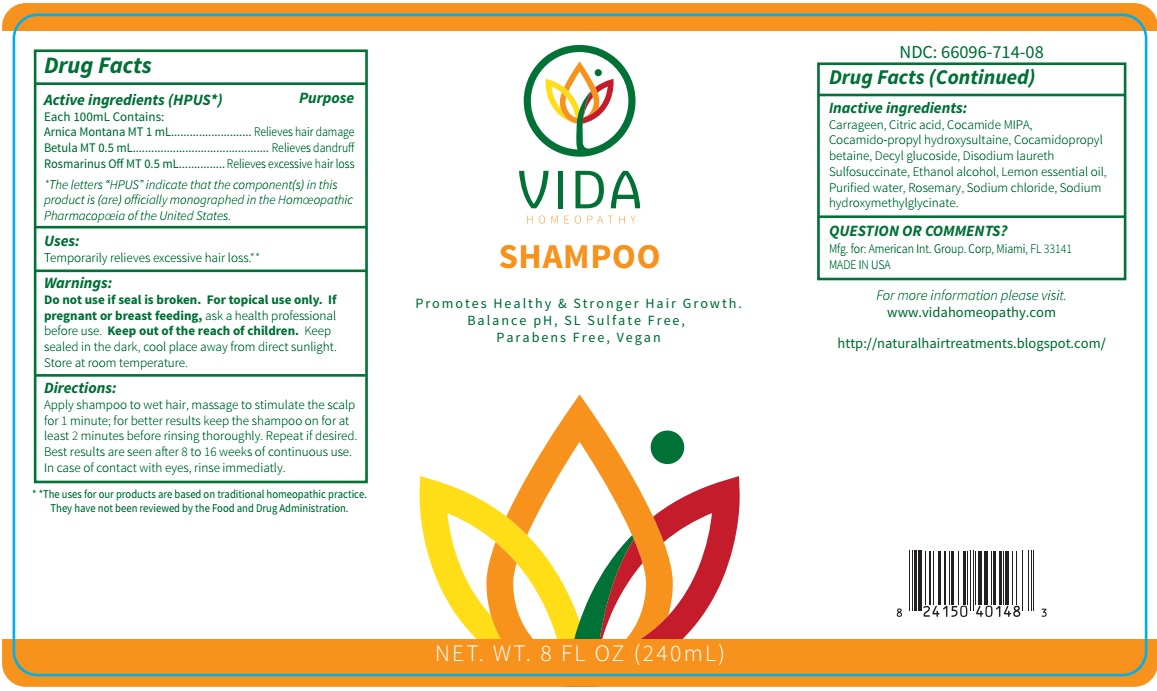 DRUG LABEL: Vida
NDC: 66096-714 | Form: SHAMPOO
Manufacturer: OHM PHARMA INC.
Category: homeopathic | Type: HUMAN OTC DRUG LABEL
Date: 20190905

ACTIVE INGREDIENTS: ARNICA MONTANA 1 [hp_X]/240 mL; ALNUS GLUTINOSA LEAF 1 [hp_X]/240 mL; ROSMARINUS OFFICINALIS FLOWERING TOP 1 [hp_X]/240 mL
INACTIVE INGREDIENTS: CHONDRUS CRISPUS; CITRIC ACID MONOHYDRATE; COCO MONOISOPROPANOLAMIDE; COCAMIDOPROPYL HYDROXYSULTAINE; COCAMIDOPROPYL BETAINE; DECYL GLUCOSIDE; DISODIUM LAURETH SULFOSUCCINATE; ALCOHOL; LEMON OIL; WATER; ROSEMARY; SODIUM CHLORIDE; SODIUM HYDROXYMETHYLGLYCINATE

Vida Shampoo

Active ingredients (HPUS*) Purpose

Each 100mL Contains:

Arnica Montana MT 1 mL............................................Relieves hair damage

Betula MT 0.5 mL..............................................................Relieves dandruff

Rosmarinus Off MT 0.5 mL................................Relieves excessive hair loss

*The letters *HPUS* indicate that the component(s) in this product is (are) officially monographed in the Homeopathic Pharmacopeia of the United States.

INDICATIONS AND USAGE

Uses: Temporarily relieves excessive hair loss.**

**The uses for our products are based on traditional homeopathic practice. They have not been reviewed by the Food and Drug Administration.

WARNINGS

Warnings: For topical use only. If pregnant or breast feeding, ask a health professional before use. Keep sealed in the dark, cool place away from direct sunlight. Store at room temperature.

- KEEP OUT OF REACH OF CHILDREN.

DOSAGE AND ADMINISTRATION

Directions: Apply shampoo to wet hair, massage to stimulate the scalp for 1 minute; for better results keep the shampoo on for at least 2 minutes before rinsing thoroughly. Repeat if desired. Best results are seen after 8 to 16 weeks of continuous use. In case of contact with eyes, rinse immediatly.

Do not use if seal is broken.

INACTIVE INGREDIENT

Inactive ingredients: Carrageen, Citric acid, Cocamide MIPA, Cocamido-propyl hydroxysultaine, Cocamidopropyl betaine, Decyl glucoside, Disodium laureth Sulfosuccinate,Ethanol alcohol, Lemon essential oil, Purified water,Rosemary, Sodium Chloride, Sodium hydroxymethylglycinate.

QUESTIONS

QUESTION OR COMMENTS?

Mfg. for: American Int. Group. Corp, Miami, FL 33141

MADE IN USA

For more information please visit. www.vidahomeopathy.com

http://naturalhairtreatments.blogspot.com/

PACKAGE LABEL

NDC: 66096-714-08

VIDA HOMEOPATHY

Shampoo

Promotes Healthy & Stronger Hair Growth.

Balance pH, SL Sulfate Free,

Parabens Free, Vegan

NET. WT. 8 FL OZ (240mL)

PURPOSE

Relieves excessive hair loss.